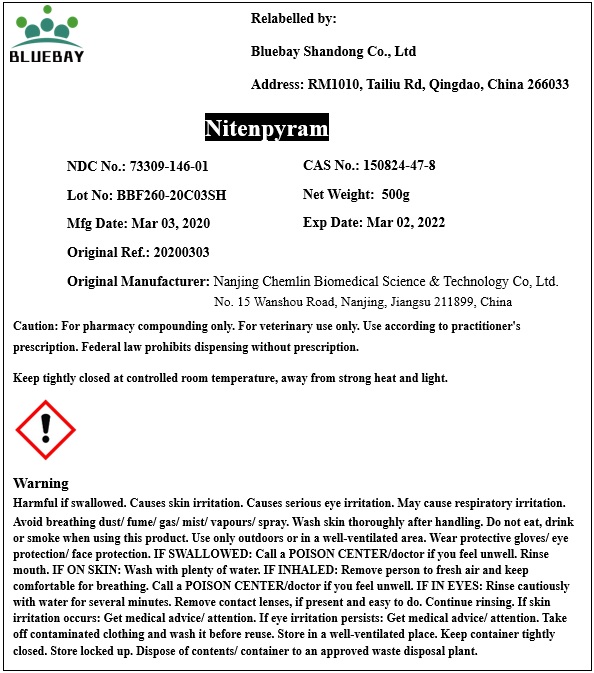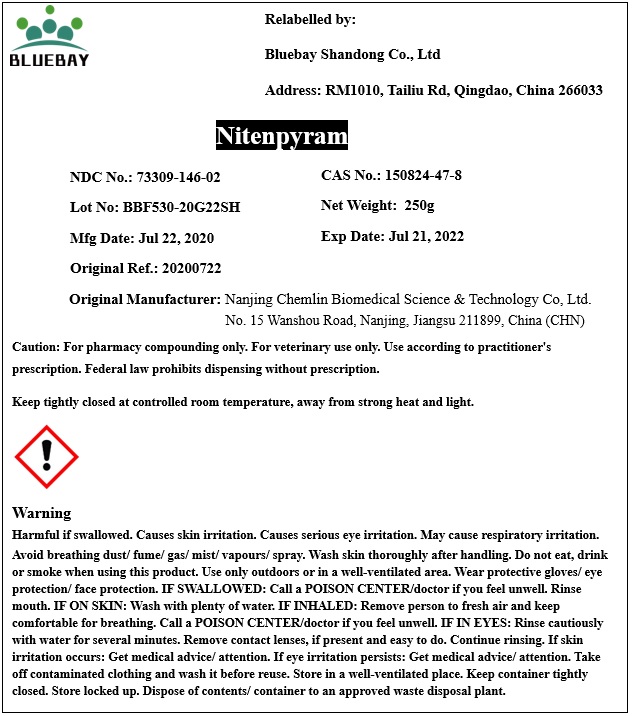 DRUG LABEL: Nitenpyram
NDC: 73309-146 | Form: POWDER
Manufacturer: BLUEBAY SHANDONG CO.,LTD
Category: other | Type: BULK INGREDIENT
Date: 20201029

ACTIVE INGREDIENTS: NITENPYRAM 1 g/1 g

Nitenpyram